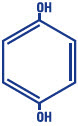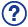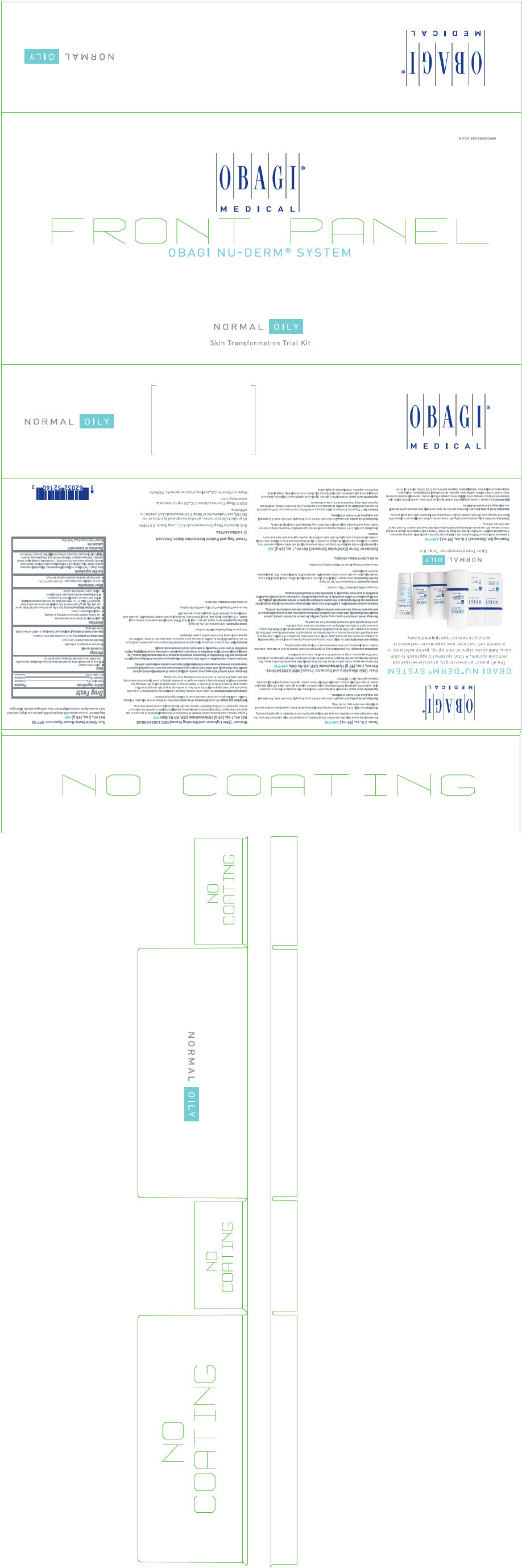 DRUG LABEL: NU-DERM system NORMAL-oily 
NDC: 62032-533 | Form: KIT | Route: TOPICAL
Manufacturer: OBAGI COSMECEUTICAL LLC
Category: prescription | Type: HUMAN PRESCRIPTION DRUG LABEL
Date: 20250314

ACTIVE INGREDIENTS: HYDROQUINONE 40 mg/1 g; HYDROQUINONE 40 mg/1 g; HOMOSALATE 100 mg/1 g; OCTISALATE 50 mg/1 g; ZINC OXIDE 165 mg/1 g
INACTIVE INGREDIENTS: EDETATE DISODIUM; BUTYLPARABEN; STEARYL ALCOHOL; SODIUM LAURYL SULFATE; CETYL ALCOHOL; GLYCERIN; LACTIC ACID, UNSPECIFIED FORM; .ALPHA.-TOCOPHEROL ACETATE; ASCORBIC ACID; SODIUM METABISULFITE; WATER; METHYLPARABEN; PROPYLPARABEN; BUTYLATED HYDROXYTOLUENE; EDETATE DISODIUM; PPG-2 MYRISTYL ETHER PROPIONATE; TROLAMINE SALICYLATE; SODIUM LAURYL SULFATE; CETYL ALCOHOL; GLYCERIN; LACTIC ACID, UNSPECIFIED FORM; .ALPHA.-TOCOPHEROL ACETATE; ASCORBIC ACID; SODIUM METABISULFITE; WATER; METHYLPARABEN; PROPYLPARABEN; BUTYLATED HYDROXYTOLUENE; PHENYL TRIMETHICONE; WATER; GLYCERIN; Hydroxyacetophenone; XANTHAN GUM; Sodium Chloride; Sodium Hydroxide; OCTYLDODECYL NEOPENTANOATE; TRIETHOXYCAPRYLYLSILANE; C15-19 Alkane; Disteardimonium Hectorite; POLYGLYCERYL-2 ISOSTEARATE; Sorbitan Olivate; DIMETHICONE; 1,2-HEXANEDIOL; CAPRYLYL GLYCOL; EDETATE DISODIUM; Candelilla Wax; Yellow Wax; POLYMETHYLSILSESQUIOXANE (4.5 MICRONS); Silicon Dioxide

OBAGI NU-DERM® SYSTEM

OBAGI NU-DERM®

Rx only

For external use only

DESCRIPTION

Hydroquinone, USP 4% is 1, 4-benzenediol. The drug is freely soluble in water and in alcohol. Chemically, hydroquinone is designated as p-dihydroxybenzene; the empirical formula is C6H6O2; molecular weight is 110.11 g/mol. The chemical structure is in the diagram below.

C6H6O2

Each gram of Obagi Nu-Derm® Clear contains:

ACTIVE: Hydroquinone, USP 4% (40 mg/g)

INACTIVES: ascorbic acid, BHT, butylparaben, cetyl alcohol, disodium EDTA, glycerin, lactic acid, methylparaben, propylparaben, saponins, sodium lauryl sulfate, sodium metabisulfite, stearyl alcohol, tocopheryl acetate, water (aqua)

Each gram of Obagi Nu-Derm Blender® contains:

ACTIVE: Hydroquinone, USP 4% (40 mg/g)

INACTIVES: ascorbic acid, BHT, cetyl alcohol, disodium EDTA, glycerin, lactic acid, methylparaben, phenyl trimethicone, PPG-2 myristyl ether propionate, propylparaben, saponins, sodium lauryl sulfate, sodium metabisulfite, TEA-salicylate, tocopheryl acetate, water (aqua)

Each gram of Obagi Nu-Derm® Sunfader® contains:

ACTIVES: Hydroquinone, USP 4% (40mg/g); Octinoxate, USP 7.5%; Oxybenzone, USP 5.5%

INACTIVES: ascorbic acid, BHT, butylparaben, cetyl alcohol, disodium EDTA, glycerin, methylparaben, propylparaben, saponins, sodium lauryl sulfate, sodium metabisulfite, stearyl alcohol, tocopheryl acetate, water (aqua)

CLINICAL PHARMACOLOGY

Topical application of hydroquinone produces a reversible depigmentation of the skin by inhibition of the enzymatic oxidation of tyrosine to 3, 4-dihydroxyphenylalanine (DOPA) and suppression of other melanocyte metabolic processes. Exposure to sunlight or ultraviolet light will cause repigmentation of the bleached areas, which may be prevented by the use of sunscreen agents such as those contained in Obagi Nu-Derm Sunfader® and Obagi Nu-Derm® Sun Shield Matte Broad Spectrum SPF 50.

INDICATIONS AND USAGE

For the gradual bleaching of hyperpigmented skin conditions such as chloasma, melasma, freckles, senile lentigines and other unwanted areas of melanin hyperpigmentation.

CONTRAINDICATIONS

People with prior history of sensitivity or allergic reaction to this product or any of its ingredients should not use it. The safety of topical hydroquinone use during pregnancy or in children (12 years and under) has not been established.

WARNINGS

Hydroquinone is a skin-bleaching agent, which may produce unwanted cosmetic effects if not used as directed. The physician should be familiar with the contents of this insert before prescribing or dispensing this product.

Test for skin sensitivity before using by applying a small amount to an unbroken patch of skin and check within 24 hours. Some users of this product may experience a mild skin irritation. If skin irritation becomes severe, stop use and consult a doctor. Close patient supervision is recommended.

WARNINGS: Avoid contact with eyes, nose, mouth and lips. In case of accidental contact, patient should rinse thoroughly with water and contact a physician. Sunscreen use is an essential aspect of hydroquinone therapy because even minimal sunlight exposure sustains melanocytic activity.

Contains sodium metabisulfite, a sulfite that may cause allergic-type reactions including anaphylactic symptoms and life-threatening or less severe asthmatic episodes in certain susceptible people. The overall prevalence of sulfite sensitivity in the general population is unknown and probably low. Sulfite sensitivity is seen more frequently in asthmatic than in nonasthmatic people.

PRECAUTIONS

(also see WARNINGS):

Treatment should be limited to relatively small areas of the body at one time since some patients experience a transient skin reddening and a mild burning sensation, which does not preclude treatment.

PREGNANCY CATEGORY C

Animal reproduction studies have not been conducted with topical hydroquinone. It is also not known whether hydroquinone can cause fetal harm when used topically on a pregnant woman or affect reproductive capacity. It is not known to what degree, if any, topical hydroquinone is absorbed systemically. Topical hydroquinone should be used on pregnant women only when clearly indicated.

NURSING MOTHERS

It is not known whether topical hydroquinone is absorbed or excreted in human milk. Caution is advised when topical hydroquinone is used by a nursing mother.

PEDIATRIC USAGE

Safety and effectiveness in children below the age of 12 years have not been established.

ADVERSE REACTIONS

No systemic adverse reactions have been reported. Occasional hypersensitivity (localized contact dermatitis) may occur, in which case the product should be discontinued and the physician notified immediately.

To report SUSPECTED ADVERSE REACTIONS, contact Obagi Cosmeceuticals LLC, at 1-800-636-7546 or FDA at 1-800-FDA-1088 or www.fda.gov/medwatch.

DOSAGE AND ADMINISTRATION

A thin application should be applied once or twice daily or as directed by a physician. If no improvement is seen after three (3) months of treatment, use of this product should be discontinued. Sun exposure should be limited by using a sunscreen agent or protective clothing to cover bleached skin when using and after using this product in order to prevent darkening from reoccurring.

HOW SUPPLIED

Obagi Nu-Derm® Clear is available as follows:
Net wt. 2 oz. (57 g) bottle
NDC 62032-101-36

Obagi Nu-Derm Blender® is available as follows:
Net wt. 2 oz. (57 g) bottle
NDC 62032-100-36

Net wt. 1 oz. (28 g) bottle
NDC 62032-100-10

Obagi Nu-Derm Sunfader® is available as follows:
Net wt. 2 oz. (57 g) bottle
NDC 62032-116-36

STORAGE AND HANDLING

Store at controlled room temperature: 15° to 25°C (59° to 77°F). Keep out of direct sunlight.

1-800-636-7546
Manufactured for:
Obagi Cosmeceuticals LLC,
Long Beach, CA 90806

All products/brand names, whether designated by notice or not (®/TM), are trademarks of Obagi Cosmeceuticals LLC and/or its affiliates.

©2019 Obagi Cosmeceuticals LLC. All rights reserved. www.obagi.com

Revised 01/2019
9458404

Obagi Nu-Derm® Clear (Hydroquinone, USP 4%) Skin Bleaching Cream

Obagi Nu-Derm Blender® (Hydroquinone, USP 4%) Skin Bleaching Cream

Obagi Nu-Derm Sunfader® (Hydroquinone, USP 4%; Octinoxate, USP 7.5%; Oxybenzone, USP 5.5%) Skin Bleaching Cream with Sunscreens

Sun Shield Matte Broad Spectrum SPF 50
Net wt. 1 oz. (28 g) AM

Drug Facts

ACTIVE INGREDIENT

Active ingredients | Purpose
Homosalate 10% | Sunscreen
Octisalate 5% | Sunscreen
Zinc Oxide 16.5% | Sunscreen

Uses

- helps prevent sunburn
- If used as directed with other sun protection measures (see Directions), decreases the risk of skin cancer and early skin aging caused by the sun

Warnings

For external use only

Do not use on damaged or broken skin

Stop use and ask a doctor if rash occurs

When using this product keep out of eyes. Rinse with water to remove.

Keep out of reach of children. If swallowed, get medical help or contact a Poison Control Center right away.

Directions

- apply liberally 15 minutes before sun exposure
- use a water resistant sunscreen if swimming or sweating
- reapply at least every 2 hours
- Sun Protection Measures. Spending time in the sun increases your risk of skin cancer and early skin aging. To decrease this risk, regularly use a sunscreen with a Broad Spectrum SPF value of 15 or higher and other sun protection measures including:
  - limit time in the sun, especially from 10 a.m.–2 p.m.
  - wear long-sleeved shirts, pants, hats, and sunglasses
- children under 6 months: Ask a doctor

Other information

- store at controlled room temperature: 15°C–25°C (59°F–77°F)
- protect this product from excessive heat and direct sun

Inactive ingredients

Water (Aqua), C15-19 Alkane, Octyldodecyl Neopentanoate, Polymethylsilsesquioxane, Sorbitan Olivate, Silica, Polyglyceryl-6 Polyrininoleate, Sodium Chloride, Xanthan Gum, Glycerin, Hydroxyacetophenone, Disodium EDTA, 1,2-Hexanediol, Caprylyl Glycol, Sodium Hydroxide, Triethoxycaprylsilane, Polyhydroxystearic Acid, Disteardimonium Hectorite, Polyglyceryl-2 Isostearate, Euphorbia Cerifera (candelilla) Wax, Beeswax, Dimethicone

Questions or comments?

1.800.636.7546

Monday–Friday 9 a.m.–4 p.m. Pacific Time

Distributed by Obagi Cosmeceuticals LLC, Long Beach, CA 90806

PRINCIPAL DISPLAY PANEL - Kit Carton

NDC# 62032-533-60

OBAGI®
MEDICAL

OBAGI NU-DERM® SYSTEM

NORMAL OILY

Skin Transformation Trial Kit